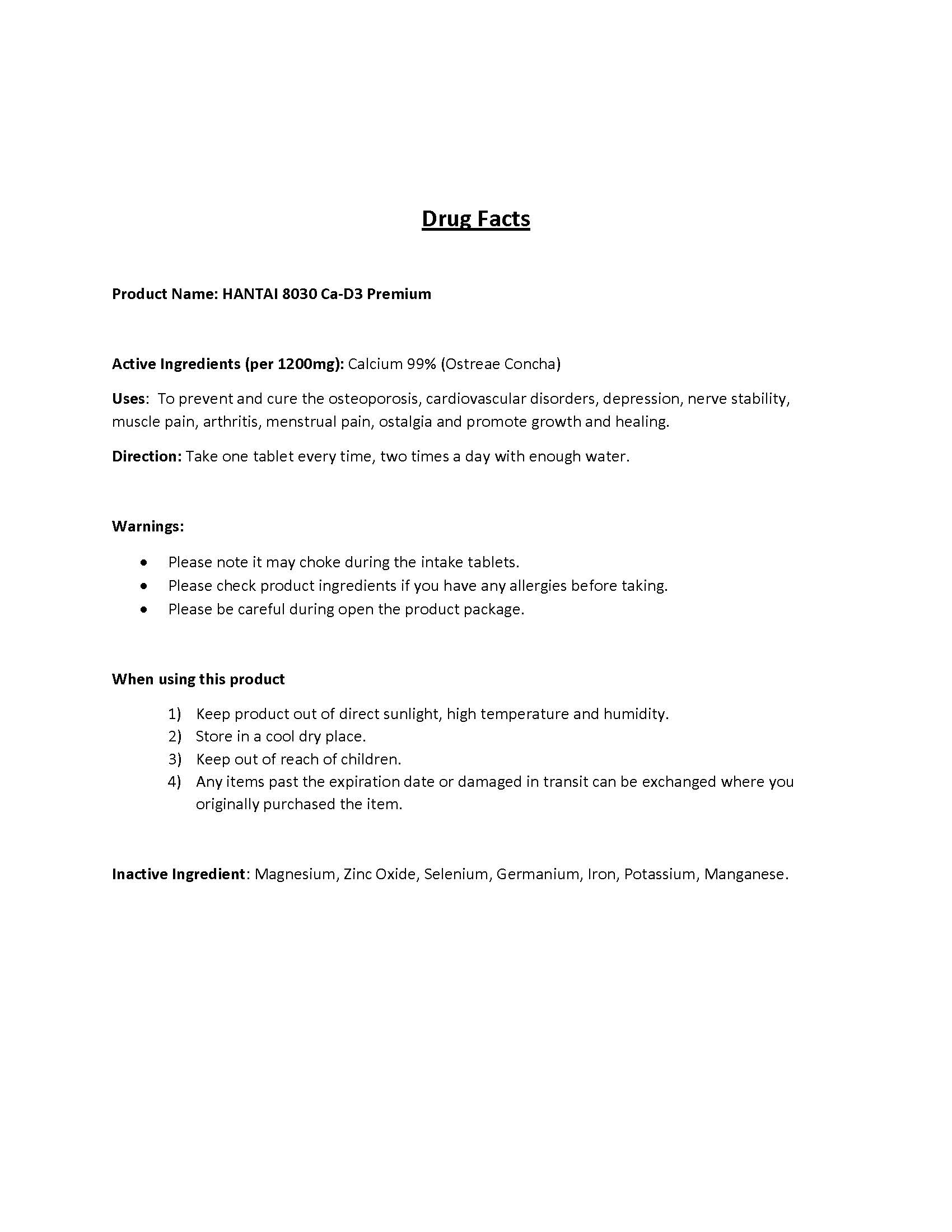 DRUG LABEL: HANTAI 8030 Ca-D3 Premium
NDC: 55259-1113 | Form: TABLET
Manufacturer: APEXEL CO., LTD.
Category: otc | Type: HUMAN OTC DRUG LABEL
Date: 20240220

ACTIVE INGREDIENTS: CALCIUM 0.99 mg/1 1
INACTIVE INGREDIENTS: ZINC OXIDE; MAGNESIUM; SELENIUM; GERMANIUM; IRON; POTASSIUM; MANGANESE

ACTIVE INGREDIENT

Ostreae Concha (Calcium 99%)

INACTIVE INGREDIENT

Magnesium, Zinc Oxide, Selenium, Germanium, Iron, Potassium, Manganese

PURPOSE

To prevent and cure the osteoporosis, cardiovascular disorders, depression, nerve stability, muscle pain, arthritis, menstrual pain, ostalgia and promote growth and healing.

KEEP OUT OF REACH OF CHILDREN

WARNINGS

- Please note it may choke during the intake tablets.
- Please check product ingredients if you have any allergies before taking.
- Please be careful during open the product package.
- Keep product out of direct sunlight, high temperature and humidity.
- Store in a cool dry place.
- Keep out of reach of children.
- Any items past the expiration date or damaged in transit can be exchanged where you originally purchased the item.

DOSAGE & ADMINISTRATION

For oral use only

USES

Take one tablet every time, two times a day with enough water.